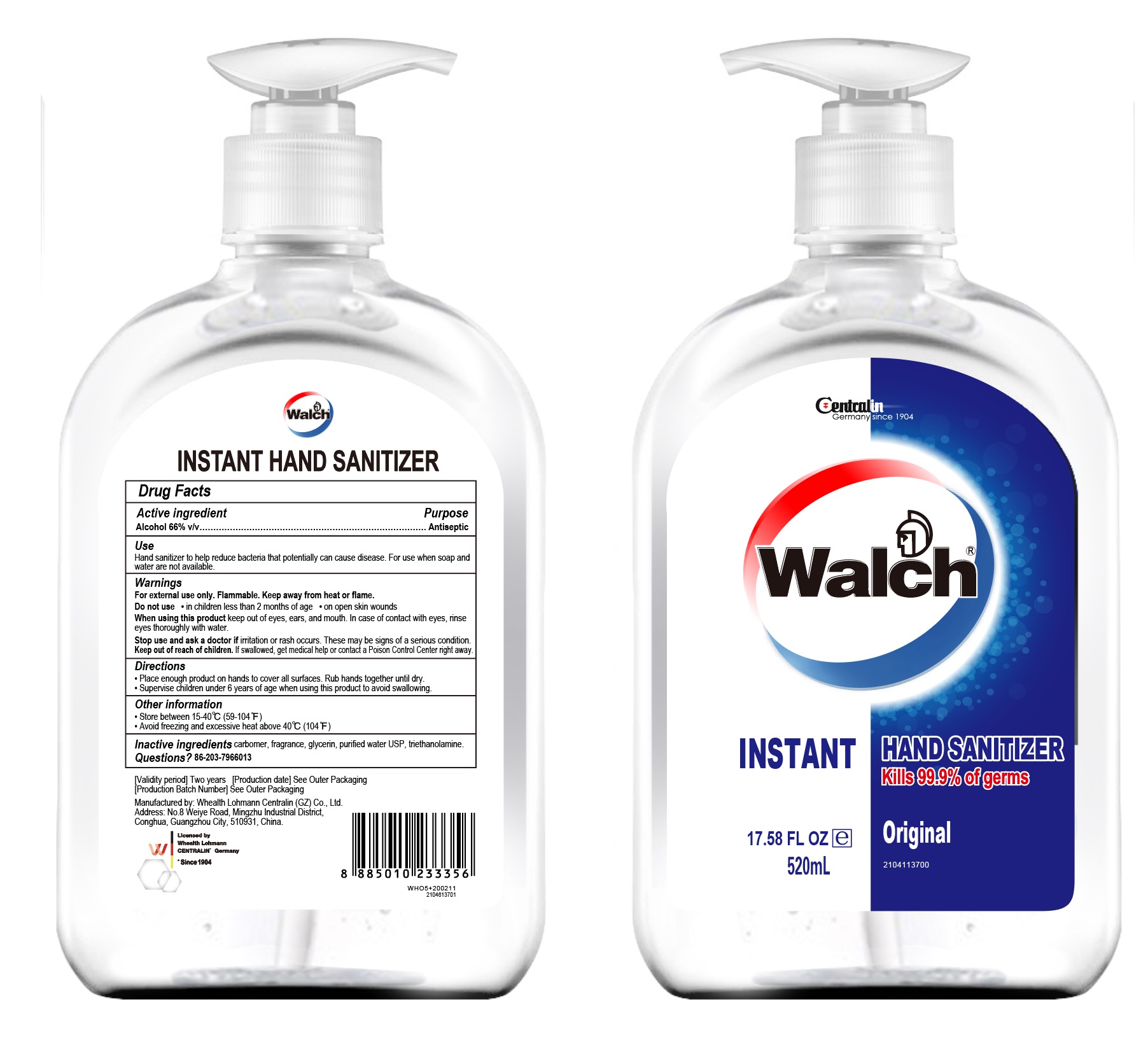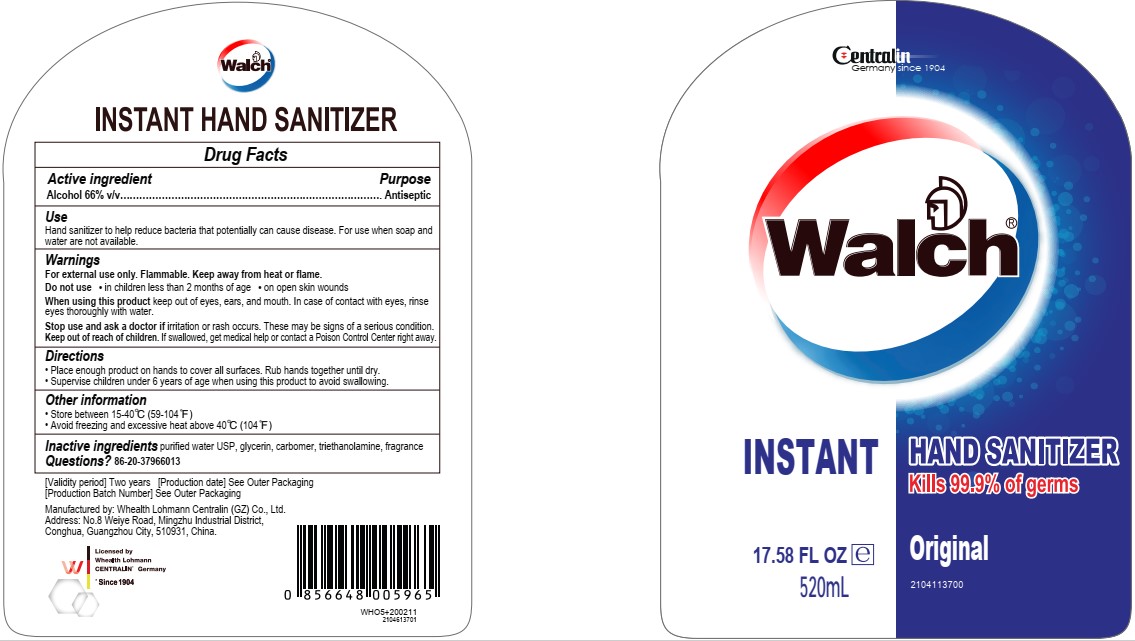 DRUG LABEL: INSTANT HAND SANITIZER
NDC: 77976-001 | Form: GEL
Manufacturer: Whealth Lohmann Centralin (GZ) Co., Ltd
Category: otc | Type: HUMAN OTC DRUG LABEL
Date: 20200710

ACTIVE INGREDIENTS: ALCOHOL 343.2 mL/520 mL
INACTIVE INGREDIENTS: FRAGRANCE LAVENDER & CHIA F-153480 0.104 mL/520 mL; TROLAMINE 0.884 mL/520 mL; GLYCERIN 5.2 mL/520 mL; CARBOMER HOMOPOLYMER TYPE B (ALLYL SUCROSE CROSSLINKED) 1.3 mL/520 mL; WATER 169.312 mL/520 mL

Active Ingredient(s)

Alcohol 66% v/v. Purpose: Antiseptic

Purpose

Antiseptic, Hand Sanitizer

Use

Hand Sanitizer to help reduce bacteria that potentially can cause disease. For use when soap and water are not available.

Warnings

For external use only. Flammable. Keep away from heat or flame

Do not use

- in children less than 2 months of age
- on open skin wounds

When using this product keep out of eyes, ears, and mouth. In case of contact with eyes, rinse eyes thoroughly with water.
Stop use and ask a doctor if irritation or rash occurs. These may be signs of a serious condition.
Keep out of reach of children. If swallowed, get medical help or contact a Poison Control Center right away.

Stop use and ask a doctor if irritation or rash occurs. These may be signs of a serious condition.

Keep out of reach of children. If swallowed, get medical help or contact a Poison Control Center right away.

Directions

- Place enough product on hands to cover all surfaces. Rub hands together until dry.
- Supervise children under 6 years of age when using this product to avoid swallowing.

Other information

- Store between 15-40C (59-104F)
- Avoid freezing and excessive heat above 40C (104F)

Inactive ingredients

carbomer, fragrance, glycerin, purified water USP, triethanolamine.

Package Label - Principal Display Panel

520 mL NDC: 77976-001-95